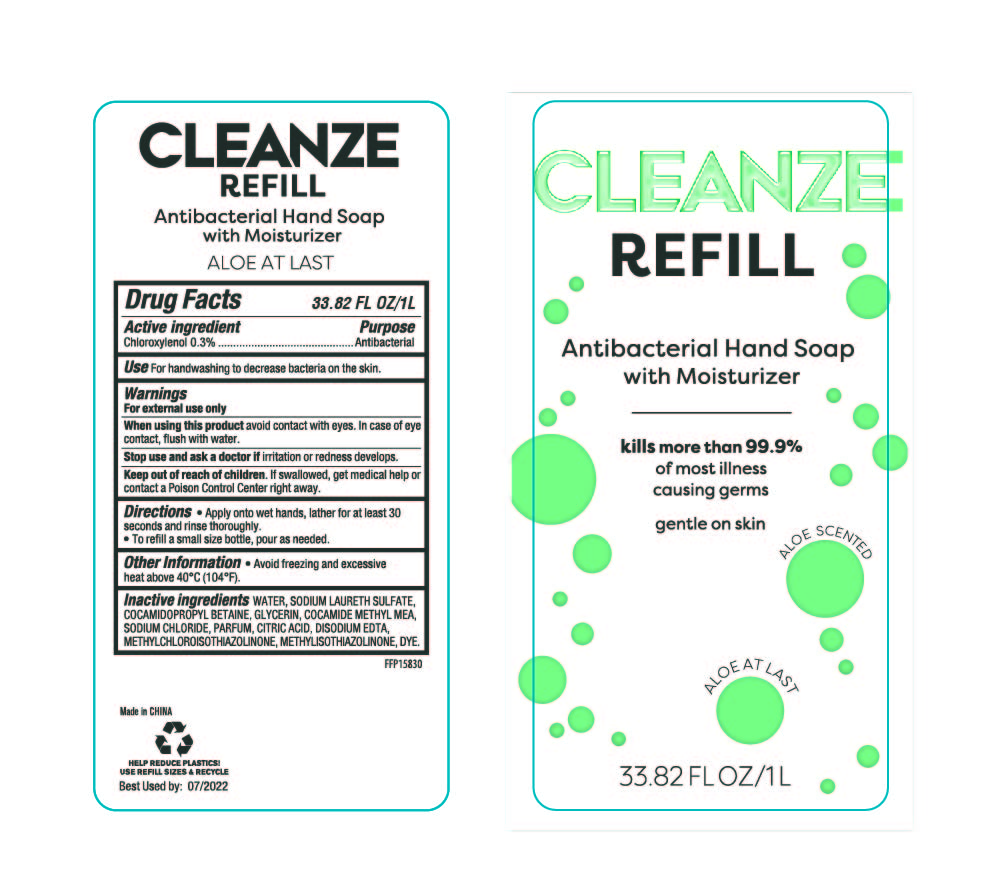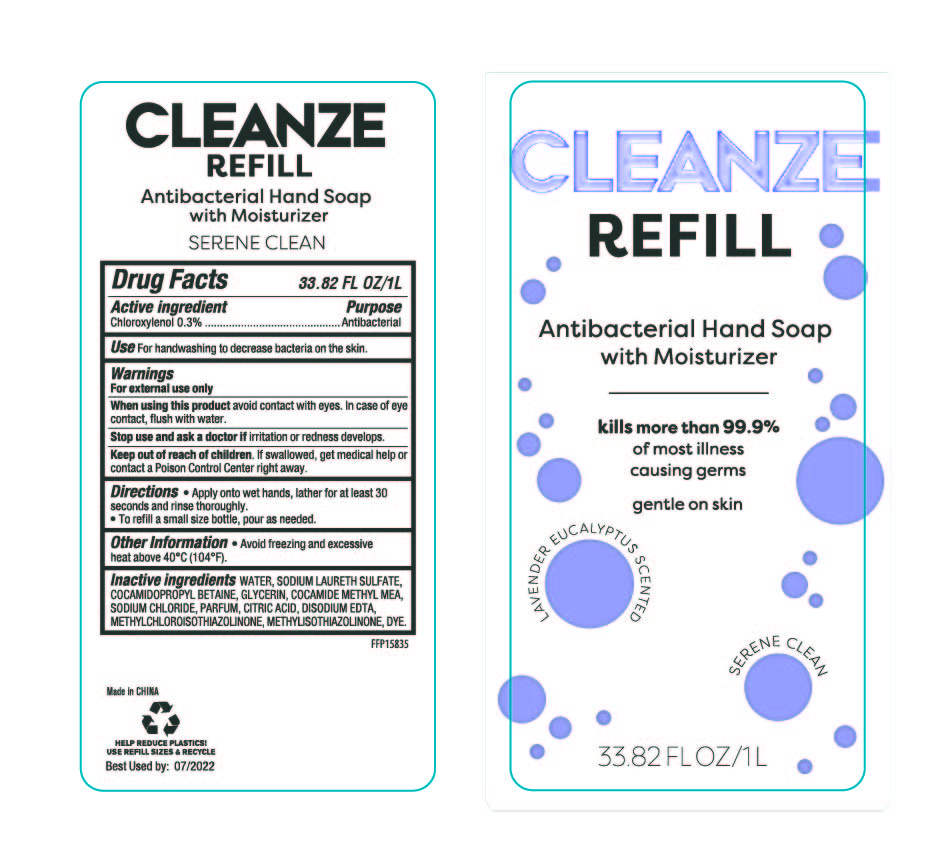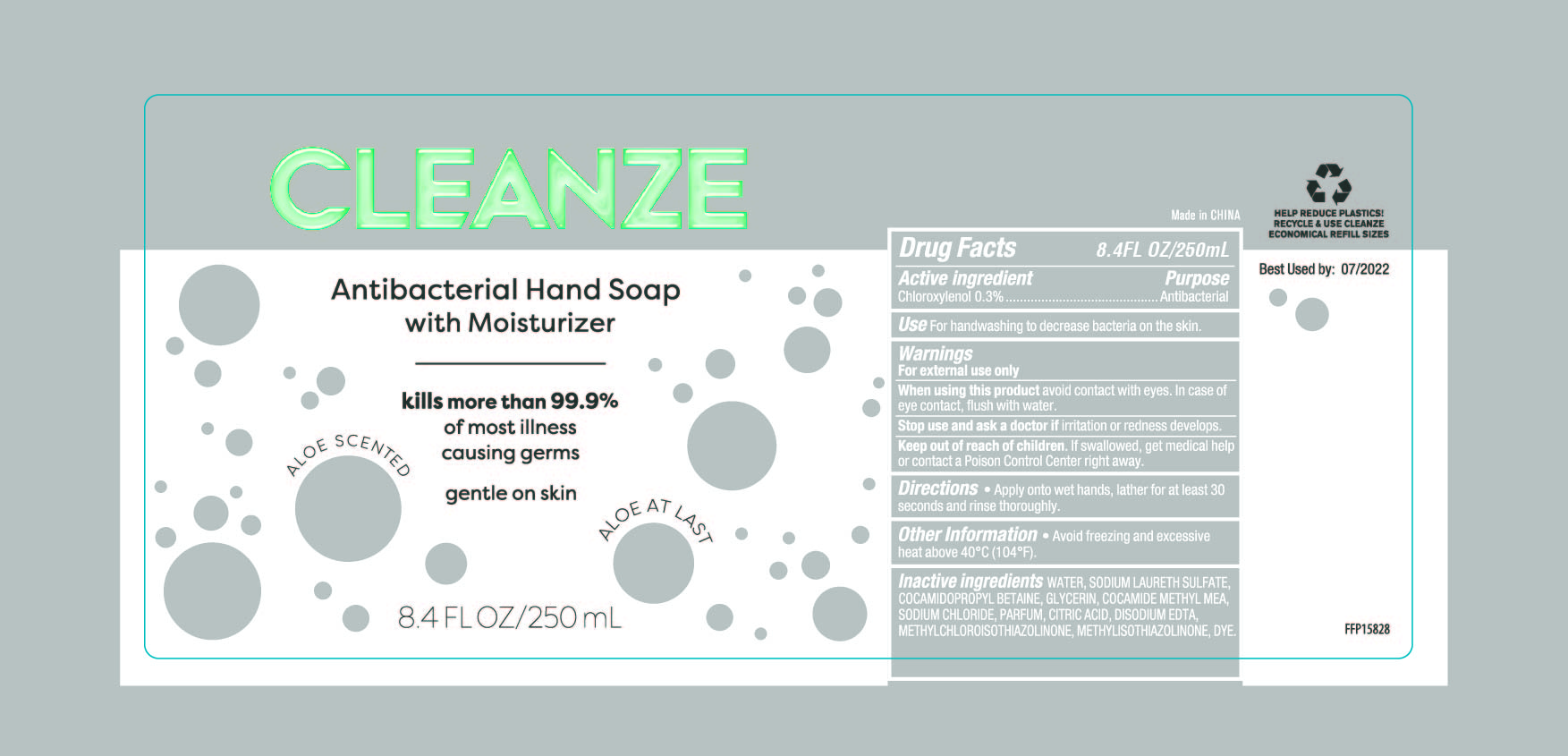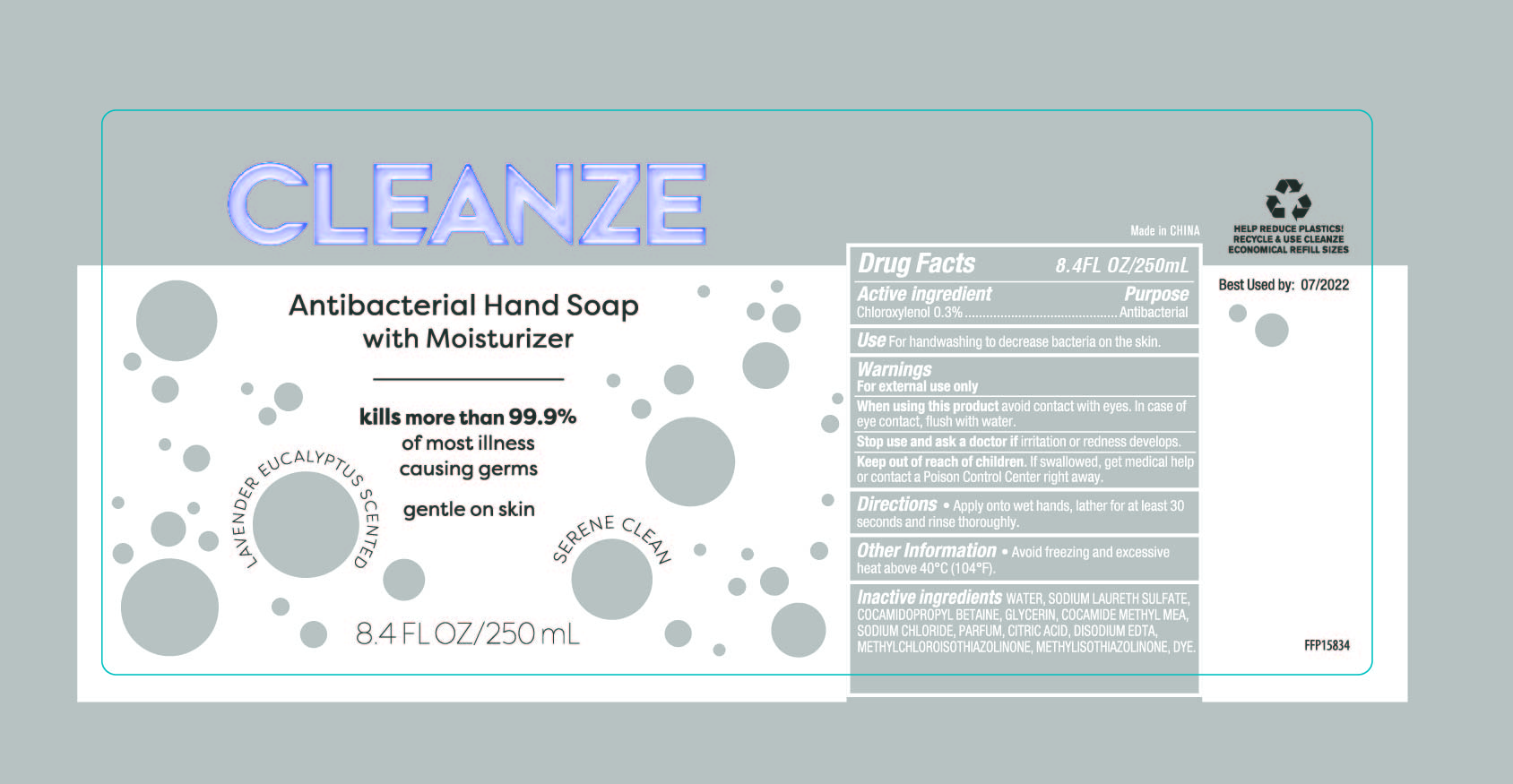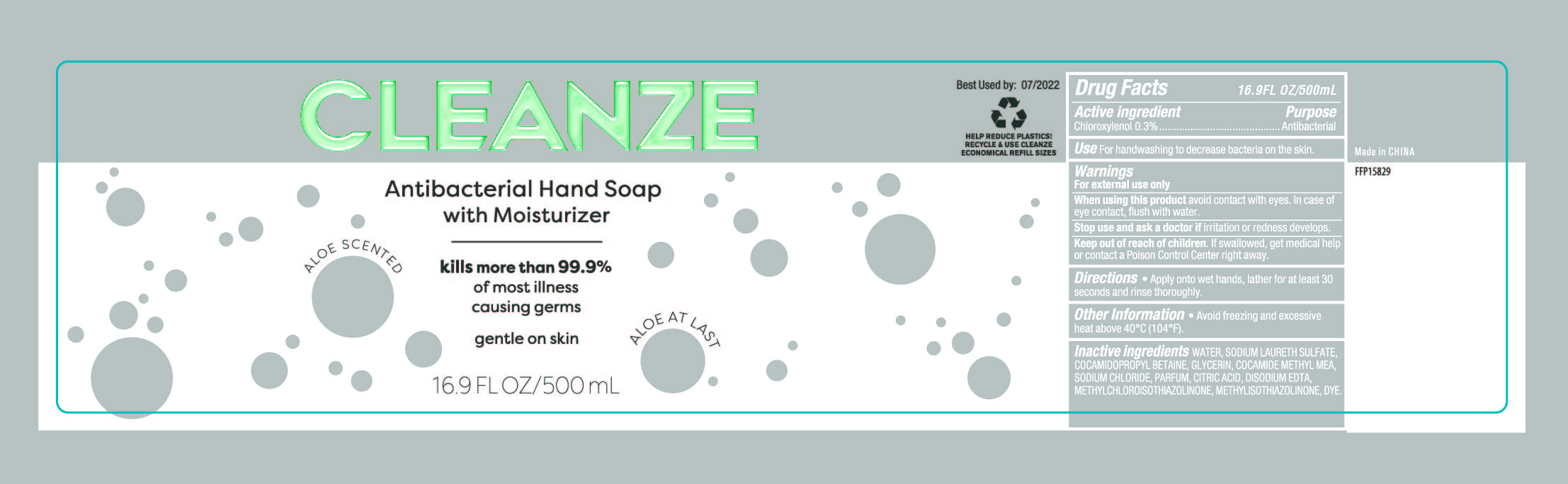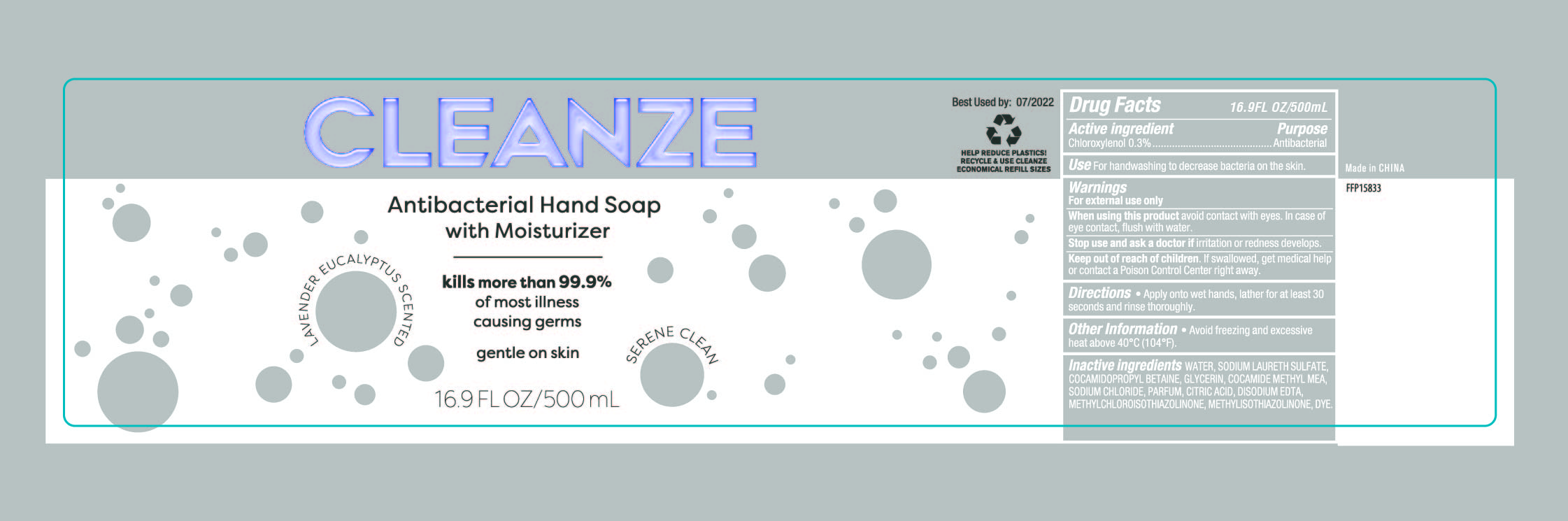 DRUG LABEL: Antibacterial HandSoap with Moisturizer
NDC: 47993-277 | Form: GEL
Manufacturer: NINGBO JIANGBEI OCEAN STAR TRADING CO.,LTD
Category: otc | Type: HUMAN OTC DRUG LABEL
Date: 20201105

ACTIVE INGREDIENTS: CHLOROXYLENOL 0.3 g/100 mL
INACTIVE INGREDIENTS: WATER; SODIUM LAURETH SULFATE; COCAMIDOPROPYL BETAINE; GLYCERIN; COCOYL METHYL MONOETHANOLAMINE; SODIUM CHLORIDE; ANHYDROUS CITRIC ACID; EDETATE DISODIUM; METHYLCHLOROISOTHIAZOLINONE; METHYLISOTHIAZOLINONE

47993-277

Active ingredients

Chloroxylenol 0.3%

PURPOSE

Antibacterial

Uses：

For hanbwashing to decrease bacteria on the skin.

Warnings:

For external use only.

When using this product avoid contact with eyes. In case of eye contact, flush with water.

Stop use and ask a doctorif irritation or redness develops.

Keep out of reach of children. If swallowed，get medical help or contact a Poison Control Center right away.

When using this product avoid contact with eyes. In case of eye contact, flush with water.

Stop use and ask a doctor if irritation or redness develops.

Keep out of reach of children. If swallowed, get medical help or contact a Poison Control Center right away.

Directions:

- Apply onto wet hands, lather for at least 30 second and rinse thoroughly.
- To refill a small size bottle, pour as needed.

Other information:

- Avoid freezing and excessive heat above 40℃(104℉).

Inactive Ingredients:

WATER, SODIUM LAURETH SULFATE, COCAMIDOPROPYL BETAINE, GLYCERIN, COCAMIDE METHYL MEA, SODIUM CHLORIDE, PARFUM, CITRIC ACID, DISODIUM EDTA, METHYLCHLOROISOTHIAZOLINONE, METHYLISOTHIAZOLINONE, DYE.